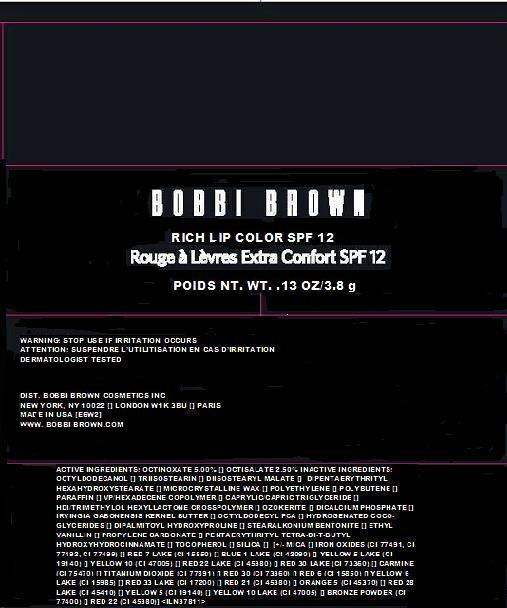 DRUG LABEL: RICH LIP COLOR
NDC: 64141-009 | Form: LIPSTICK
Manufacturer: Bobbi Brown Professional Cosmetics Inc.
Category: otc | Type: HUMAN OTC DRUG LABEL
Date: 20110606

ACTIVE INGREDIENTS: OCTINOXATE 5.0 g/100 g; OCTISALATE 2.5 g/100 g
INACTIVE INGREDIENTS: OCTYLDODECANOL; DIPENTAERYTHRITYL HEXACAPRYLATE/HEXACAPRATE ; MICROCRYSTALLINE WAX; HIGH DENSITY POLYETHYLENE; POLYBUTENE (1400 MW); PARAFFIN; MEDIUM-CHAIN TRIGLYCERIDES; ANHYDROUS DIBASIC CALCIUM PHOSPHATE; IRVINGIA GABONENSIS SEED; HYDROGENATED COCONUT OIL; DIPALMITOYL HYDROXYPROLINE; VANILLIN; PROPYLENE CARBONATE; PENTAERYTHRITOL TETRAKIS(3-(3,5-DI-TERT-BUTYL-4-HYDROXYPHENYL)PROPIONATE); TOCOPHEROL; SILICON DIOXIDE; MICA; FD&C BLUE NO. 1; FD&C YELLOW NO. 5; D&C RED NO. 7; COCHINEAL

ACTIVE INGREDIENTS: OCTINOXATE 5.00% [] OCTISALATE 2.50%

INACTIVE INGREDIENT

INACTIVE INGREDIENTS: OCTYLDODECANOL [] TRIISOSTEARIN [] DIISOSTEARYL MALATE [] DIPENTAERYTHRITYL HEXAHYDROXYSTEARATE [] MICROCRYSTALLINE WAX [] POLYETHYLENE [] POLYBUTENE [] PARAFFIN [] VP/HEXADECENE COPOLYMER [] CAPRYLIC/CAPRIC TRIGLYCERIDE [] HDI/TRIMETHYLOL HEXYLLACTONE CROSSPOLYMER [] OZOKERITE [] DICALCIUM PHOSPHATE [] IRVINGIA GABONENSIS KERNEL BUTTER [] OCTYLDODECYL PCA [] HYDROGENATED COCO-GLYCERIDES [] DIPALMITOYL HYDROXYPROLINE [] STEARALKONIUM BENTONITE [] ETHYL VANILLIN [] PROPYLENE CARBONATE [] PENTAERYTHRITYL TETRA-DI-T-BUTYL HYDROXYHYDROCINNAMATE [] TOCOPHEROL [] SILICA [] [+/- MICA [] IRON OXIDES (CI 77491, CI 77492, CI 77499) [] RED 7 LAKE (CI 15850) [] BLUE 1 LAKE (CI 42090) [] YELLOW 5 LAKE (CI 19140) [] YELLOW 10 (CI 47005) [] RED 22 LAKE (CI 45380) [] RED 30 LAKE (CI 73360) [] CARMINE (CI 75470) [] TITANIUM DIOXIDE (CI 77891) [] RED 30 (CI 73360) [] RED 6 (CI 15850) [] YELLOW 6 LAKE (CI 15985) [] RED 33 LAKE (CI 17200) [] RED 21 (CI 45380) [] ORANGE 5 (CI 45370) [] RED 28 LAKE (CI 45410) [] YELLOW 5 (CI 19140) [] YELLOW 10 LAKE (CI 47005) [] BRONZE POWDER (CI 77400) [] RED 22 (CI 45380)

WARNINGS

WARNING: STOP USE IF IRRITATION OCCURS.

PACKAGE LABEL

BOBBI BROWN

RICH LIP COLOR SPF 12

NET WT. 0.13 oz/ 3.8 g

Distr. Bobbi Brown Professional Cosmetics

New York, NY 10022